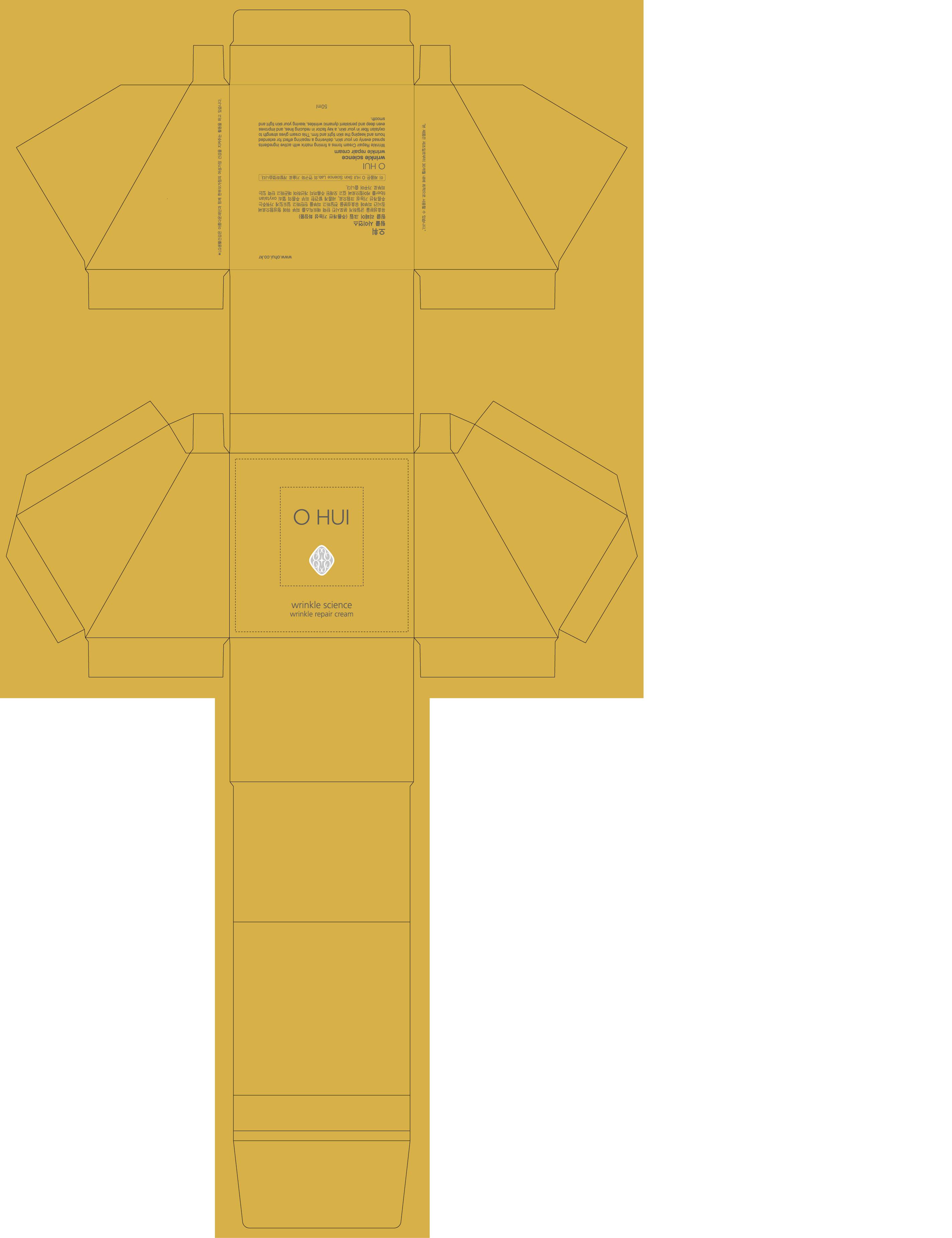 DRUG LABEL: O HUI WRINKLE SCIENCE WRINKLE REPAIR
NDC: 53208-430 | Form: CREAM
Manufacturer: LG Household and Healthcare, Inc.
Category: otc | Type: HUMAN OTC DRUG LABEL
Date: 20100604

ACTIVE INGREDIENTS: HYDROXYPROLINE 0.5 1/100 mL
INACTIVE INGREDIENTS: WATER; GLYCERIN; DIPROPYLENE GLYCOL; 2-ETHYLHEXANOIC ACID; CAPRYLIC/CAPRIC MONO/DIGLYCERIDES; CETOSTEARYL ALCOHOL; GLYCERYL MONOSTEARATE; ALCOHOL; YELLOW WAX; PANTHENOL; SORBITAN MONOSTEARATE; POLYETHYLENE GLYCOL; DIMETHICONE; METHYLPARABEN; TROLAMINE; CARBOMER 934; PROPYLPARABEN; ETHYLPARABEN; EDETATE TRISODIUM; FD&C YELLOW NO. 6; FD&C YELLOW NO. 5

DRUG FACTS

ACTIVE INGREDIENTS

HYDROXYPROLINE 0.5mL/100mL

WARNINGS AND PRECAUTIONS

For external use only.

Keep out of reach of children. Is swallowed, get medical help or contact a Poison Control Center right away.

WHEN USING

Keep out of eyes. Rinse with water to remove.

STOP USE

Stop use if a rash or irritation develops and lasts.

PACKAGE LABEL

OHUI
WRINKLE SCIENCE
WRINKLE REPAIR CREAM